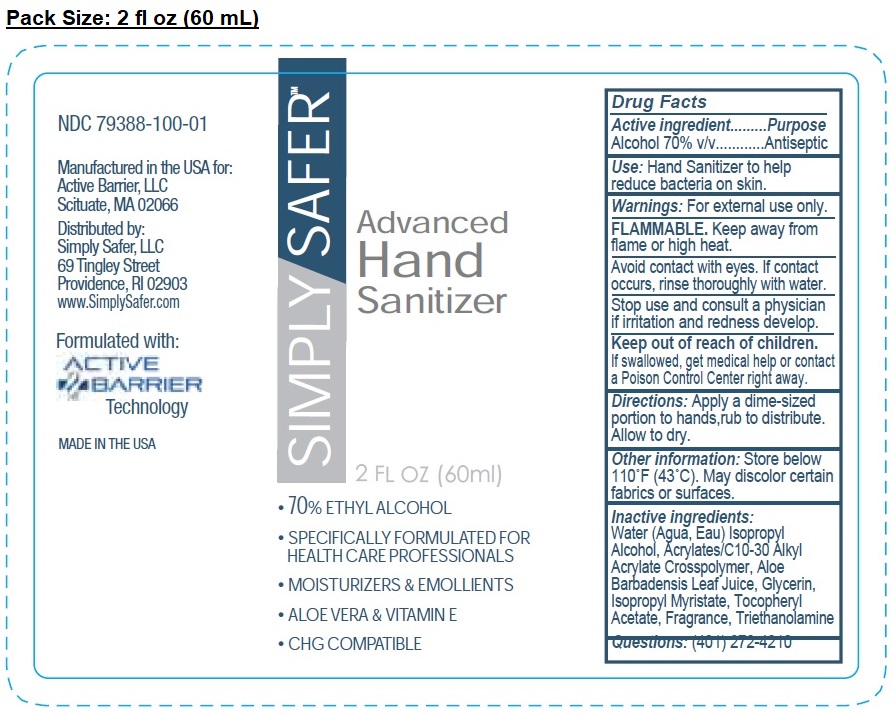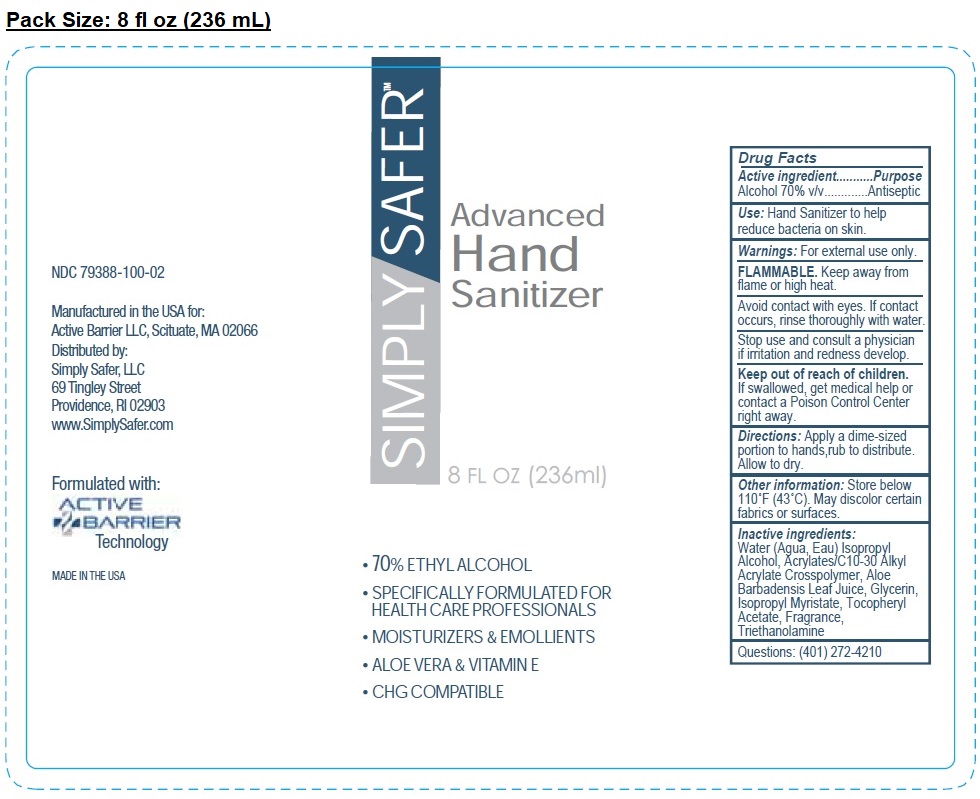 DRUG LABEL: SIMPLY SAFER ADVANCED HAND SANITIZER
NDC: 79388-100 | Form: GEL
Manufacturer: Active Barrier Llc
Category: otc | Type: HUMAN OTC DRUG LABEL
Date: 20200711

ACTIVE INGREDIENTS: ALCOHOL 70 mL/100 mL
INACTIVE INGREDIENTS: WATER; ISOPROPYL ALCOHOL; CARBOMER INTERPOLYMER TYPE A (ALLYL SUCROSE CROSSLINKED); ALOE VERA LEAF; GLYCERIN; ISOPROPYL MYRISTATE; .ALPHA.-TOCOPHEROL ACETATE; TROLAMINE

SIMPLY SAFER Advanced Hand Sanitizer

Active ingredient

Alcohol 70% v/v

Purpose

Antiseptic

INDICATIONS AND USAGE

Use: Hand Sanitizer to help reduce bacteria on skin.

Warnings: For external use only.

FLAMMABLE. Keep away from flame or high heat.

Avoid contact with eyes. If contact occurs, rinse thoroughly with water.

Stop use and consult a physician if irritation and redness develop.

Keep out of reach of children.

If swallowed, get medical help or contact a Poison Control Center right away.

DOSAGE AND ADMINISTRATION

Directions: Apply a dime-sized portion to hands, rub to distribute. Allow to dry.

Other information: Store below 110°F (43°C). May discolor certain fabrics or surfaces.

Inactive ingredients:

Water (Agua, Eau) Isopropyl Alcohol, Acrylates/C10-30 Alkyl Acrylate Crosspolymer, Aloe Barbadensis Leaf Juice, Glycerin, Isopropyl Myristate, Tocopheryl Acetate, Fragrance, Triethanolamine

Questions: (401) 272-4210

• 70% ETHYL ALCOHOL

• SPECIFICALLY FORMULATED FOR HEALTH CARE PROFESSIONALS

• MOISTURIZERS & EMOLLIENTS

• ALOE VERA & VITAMIN E

• CHG COMPATIBLE

Manufactured in the USA for:

Active Barrier, LLC,

Scituate, MA 02066

Distributed by:

Simply Safer, LLC

69 Tingley Street

Providence, RI 02903

www.SimplySaferProducts.com

Formulated with:

ACTIVE BARRIER Technology

MADE IN THE USA